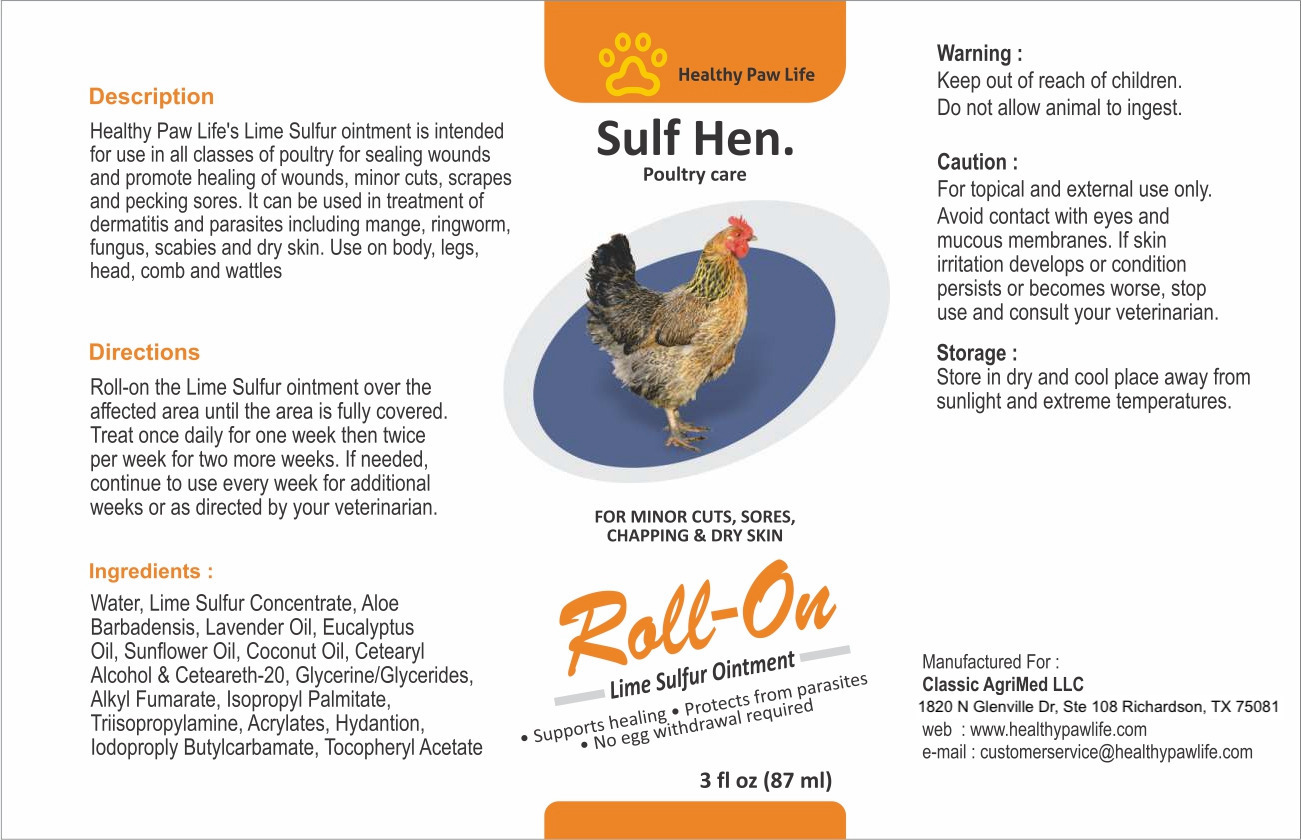 DRUG LABEL: HEALTHY PAW LIFE ROLLON POULTRY
NDC: 86130-601 | Form: LOTION
Manufacturer: CLASSIC AGRIMED LLC
Category: animal | Type: OTC ANIMAL DRUG LABEL
Date: 20231118

ACTIVE INGREDIENTS: CALCIUM POLYSULFIDE 0.32 1/100 g

HEALTHY PAW LIFE LIME SULFUR ROLLON POULTRY

SULF HEN POULTRY CARE

For Minor Cuts, Sores, Chapping & Dry Skin

Roll-On Lime Sulfur Ointment

Supports healing • Protects from parasites • No egg withdrawal required

Description:
Healthy Paw Life's Lime Sulfur ointment is intended for use in all classes of poultry for sealing wounds and promote healing of wounds, minor cuts, scrapes and pecking sores. It can be used in treatment of dermatitis and parasites including mange, ringworm, fungus, scabies and dry skin. Use on body, legs, head, comb and wattles

Warning:
Keep out of reach of children. Do not allow animal to ingest.

Storage:
Store in dry and cool place away from sunlight and extreme temperatures.

Directions:
Roll-on the Lime Sulfur ointment over the affected area until the area is fully covered.
Treat once dailv for one week then twice per week for two more weeks. If needed, continue to use every week for additional weeks or as directed by vour veterinarian.

Caution:
For topical and external use only.
Avoid contact with eyes and mucous membranes. If skin irritation develops or condition persists or becomes worse, stop use and consult your veterinarian.

Ingredients:

Water, Lime Sulfur Concentrate, Aloe Barbadensis, Lavender Oil, Eucalyptus Oil, Sunflower Oil, Coconut Oil, Cetearyl Alcohol & Ceteareth-20, Glycerine/Glycerides, Alkyl Fumarate. Isopropvl Palmitate, Trisopropylamine, Acrylates, Hydantion, lodoproply Butylcarbamate, Tocopheryl Acetate